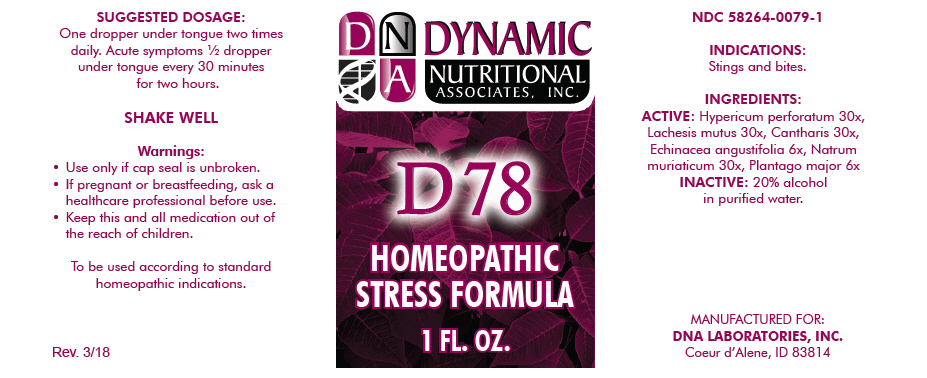 DRUG LABEL: D-78
NDC: 58264-0079 | Form: SOLUTION
Manufacturer: DNA Labs, Inc.
Category: homeopathic | Type: HUMAN OTC DRUG LABEL
Date: 20250113

ACTIVE INGREDIENTS: HYPERICUM PERFORATUM 30 [hp_X]/1 mL; LACHESIS MUTA VENOM 30 [hp_X]/1 mL; LYTTA VESICATORIA 30 [hp_X]/1 mL; ECHINACEA ANGUSTIFOLIA 6 [hp_X]/1 mL; SODIUM CHLORIDE 30 [hp_X]/1 mL; PLANTAGO MAJOR 6 [hp_X]/1 mL
INACTIVE INGREDIENTS: ALCOHOL; WATER

D-78

NDC 58264-0079-1

INDICATIONS

PURPOSE

Stings and bites.

INGREDIENTS

ACTIVE

Hypericum perforatum 30x, Lachesis mutus 30x, Cantharis 30x, Echinacea angustifolia 6x, Natrum muriaticum 30x, Plantago major 6x

INACTIVE

20% alcohol in purified water.

SUGGESTED DOSAGE

One dropper under tongue two times daily. Acute symptoms ½ dropper under tongue every 30 minutes for two hours.

STORAGE AND HANDLING

SHAKE WELL

Warnings

- Use only if cap seal is unbroken.

PREGNANCY OR BREAST FEEDING

- If pregnant or breastfeeding, ask a healthcare professional before use.

KEEP OUT OF REACH OF CHILDREN

- Keep this and all medication out of the reach of children.

To be used according to standard homeopathic indications.

PRINCIPAL DISPLAY PANEL - 1 FL. OZ. Bottle Label

DYNAMIC
NUTRITIONAL
ASSOCIATES, INC.

D 78

HOMEOPATHIC
STRESS FORMULA

1 FL. OZ.